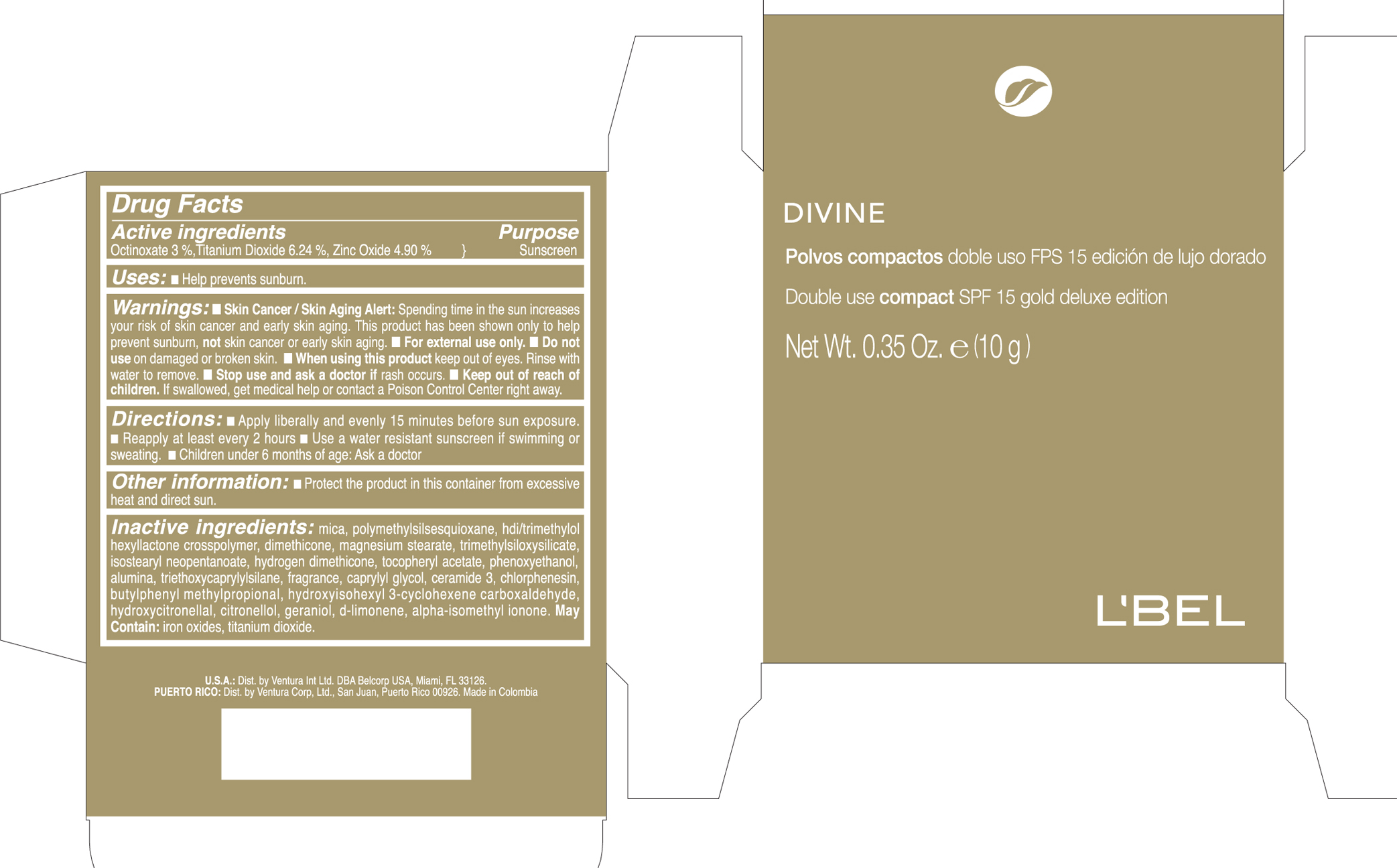 DRUG LABEL: LBEL 
NDC: 14141-499 | Form: POWDER
Manufacturer: Bel Star S.A. (Colombia)
Category: otc | Type: HUMAN OTC DRUG LABEL
Date: 20191119

ACTIVE INGREDIENTS: Titanium Dioxide 0.0624 g/1 g; Zinc Oxide 0.049 g/1 g; Octinoxate 0.03 g/1 g
INACTIVE INGREDIENTS: MICA; DIMETHICONE; MAGNESIUM STEARATE; ISOSTEARYL NEOPENTANOATE; .ALPHA.-TOCOPHEROL ACETATE; PHENOXYETHANOL; ALUMINUM OXIDE; TRIETHOXYCAPRYLYLSILANE; CAPRYLYL GLYCOL; CERAMIDE 3; CHLORPHENESIN; FERRIC OXIDE YELLOW; FERRIC OXIDE RED; FERROSOFERRIC OXIDE

L'BEL
DIVINE Polvos compactos doble uso FPS 15 edición de lujo dorado/Double use compact SPF 15 gold deluxe edition

Drug Facts

Active ingredients Purpose
TITANIUM DIOXIDE (6.24%) Sunscreen

ZINC OXIDE (4.9%) Sunscreen

OCTINOXATE (3.0%) Sunscreen

uses

- Help prevents sunburn

Keep out of reach of children. If swallowed, get medical help or contact a Poison Control Center right away.

Stop use and ask a doctor if rash occurs.

WARNINGS

Skin Cancer / Skin Aging Alert; Spending time in the sun increases your risk of skin cancer and early skin aging. This product has been shown only to help prevent sunburn, not skin cancer or early skin aging.

- For external use only.
- Do not use on damage or broken skin.
- When using this product keep out of eyes. Rinse with water to remove.

DOSAGE AND ADMINISTRATION

Apply liberally and evenly 15 minutes before sun exposure.
Reapply at least every 2 hours.
Use a water resistant sunscreen if swimming or sweating.

Children under 6 months of age: Ask a doctor.

Inactive ingredients
MICA, POLYMETHYLSILSESQUIOXANE, HDI/TRIMETHYLOL HEXYLLACTONE CROSSPOLYMER, DIMETHICONE,
MAGNESIUM STEARATE, TRIMETHYLSILOXYSILICATE, ISOSTEARYL NEOPENTANOATE, HYDROGEN DIMETHICONE,
TOCOPHERYL ACETATE, PHENOXYETHANOL, ALUMINA, TRIETHOXYCAPRYLYLSILANE, PARFUM (FRAGRANCE),
CAPRYLYL GLYCOL, CERAMIDE 3, CHLORPHENESIN. MAY CONTAIN: CI 77492 (IRON OXIDES),
CI 77491 (IRON OXIDES), CI 77891 (TITANIUM DIOXIDE), CI 77499 (IRON OXIDES).

PRINCIPAL DISPLAY PANEL - 10 g Cartridge Box - Claire 1-2-3

DIVINE

Polvos compactos doble uso FPS 15 edición de lujo dorado

Double use compact SPF 15 gold deluxe edition

Net Wt. 0.35 oz. e (10 g)

L'BEL

PRINCIPAL DISPLAY PANEL - 10 g Cartridge Box - Claire 4

DIVINE

Polvos compactos doble uso FPS 15 edición de lujo dorado

Double use compact SPF 15 gold deluxe edition

Net Wt. 0.35 oz. e (10 g)

L'BEL

PRINCIPAL DISPLAY PANEL - 10 g Cartridge Box - Medium 5

DIVINE

Polvos compactos doble uso FPS 15 edición de lujo dorado

Double use compact SPF 15 gold deluxe edition

Net Wt. 0.35 oz. e (10 g)

L'BEL

PRINCIPAL DISPLAY PANEL - 10 g Cartridge Box - Medium 6

DIVINE

Polvos compactos doble uso FPS 15 edición de lujo dorado

Double use compact SPF 15 gold deluxe edition

Net Wt. 0.35 oz. e (10 g)

L'BEL

PRINCIPAL DISPLAY PANEL - 10 g Cartridge Box - Medium 7

DIVINE

Polvos compactos doble uso FPS 15 edición de lujo dorado

Double use compact SPF 15 gold deluxe edition

Net Wt. 0.35 oz. e (10 g)

L'BEL

PRINCIPAL DISPLAY PANEL - 10 g Cartridge Box - Obscure 8-9

DIVINE

Polvos compactos doble uso FPS 15 edición de lujo dorado

Double use compact SPF 15 gold deluxe edition

Net Wt. 0.35 oz. e (10 g)

L'BEL